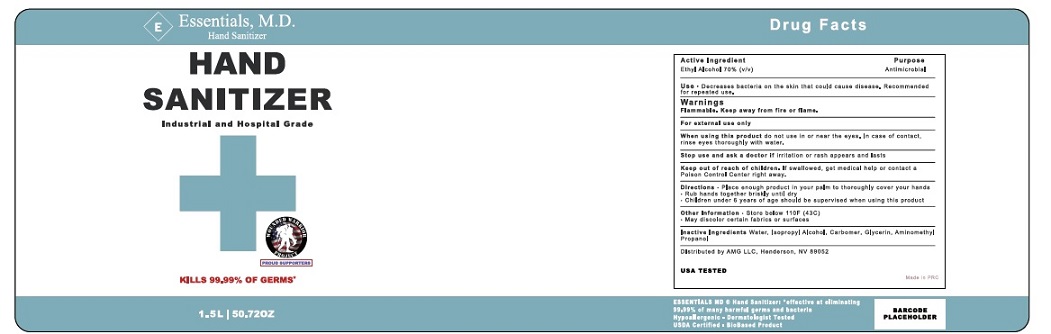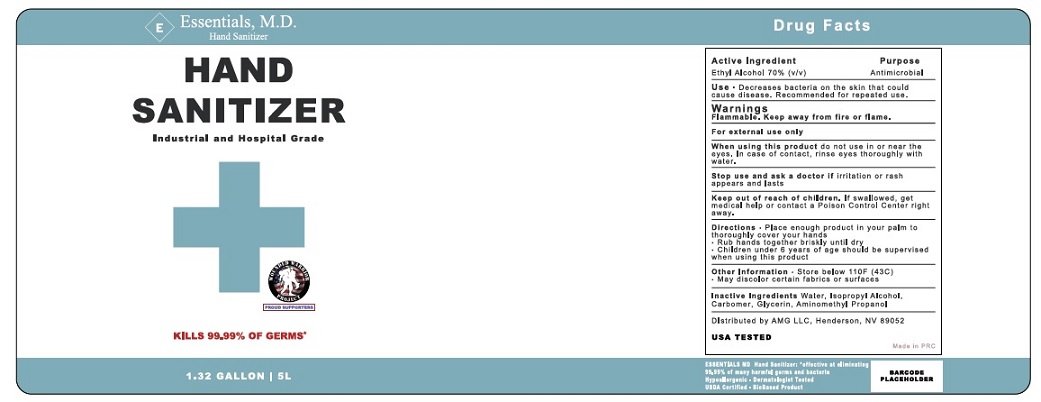 DRUG LABEL: Essentials, M.D. Hand sanitizer
NDC: 77205-002 | Form: GEL
Manufacturer: ALLEN-MEYER GROUP LLC
Category: otc | Type: HUMAN OTC DRUG LABEL
Date: 20200630

ACTIVE INGREDIENTS: ALCOHOL 70 mL/100 mL
INACTIVE INGREDIENTS: WATER; ISOPROPYL ALCOHOL; AMINOMETHYLPROPANOL; GLYCERIN; CARBOMER HOMOPOLYMER, UNSPECIFIED TYPE

Active Ingredient

Ethyl Alcohol 70% v/v.

Purpose

Antimicrobial

Uses

Hand Sanitizer to help reduce bacteria that potentially can cause disease.

Reccomended for repeated use.

Warnings

Flammable. Keep away from heat or flame.

For external use only.

When using this product do not use in or near the eyes. In case of contact with eyes, rinse eyes thoroughly with water.

Stop use and ask a doctor if irritation or rash appears and lasts.

Keep out of reach of children. If swallowed, get medical help or contact a Poison Control Center right away.

Directions

- Place enough product on hands to thoroughly cover your hands. Rub hands together briskly until dry.
- Children under 6 years of age should be supervised when using this product.

Other information

- Store below 110 F (43C).
- May discolor certain fabrics or surfaces.

Inactive ingredients

Water, Isopropyl alcohol, Carbomer, Glycerin, Aminomethy Propanol.